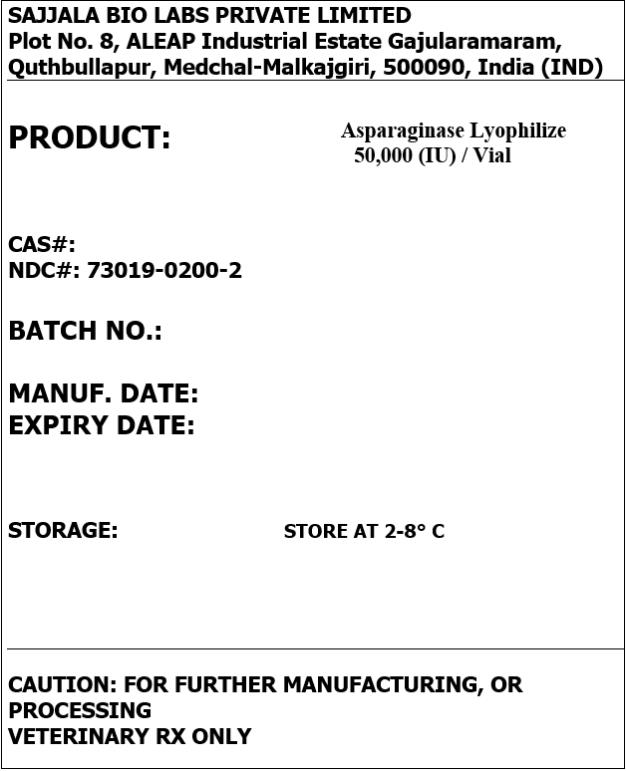 DRUG LABEL: Asparaginase Lyophilized
NDC: 73019-0200 | Form: POWDER
Manufacturer: SAJJALA BIO LABS PRIVATE LIMITED
Category: other | Type: BULK INGREDIENT
Date: 20210504

ACTIVE INGREDIENTS: ASPARAGINASE 1 [iU]/1 [iU]

Asparaginase Lyophilized

PRINCIPAL DISPLAY PANEL – BULK PRODUCT

SAJJALA BIO LABS PRIVATE LIMITED
Plot No. 8, ALEAP Industrial Estate Gajularamaram, Quthbullapur, Medchal-Malkajgiri, 500090, India (IND)

PRODUCT: Asparaginase Lyophilized 50,000 (IU) / Vial

NDC#: 73019-0200-2

CAUTION: FOR FURTHER MANUFACTURING, OR PROCESSING
VETERINARY RX ONLY